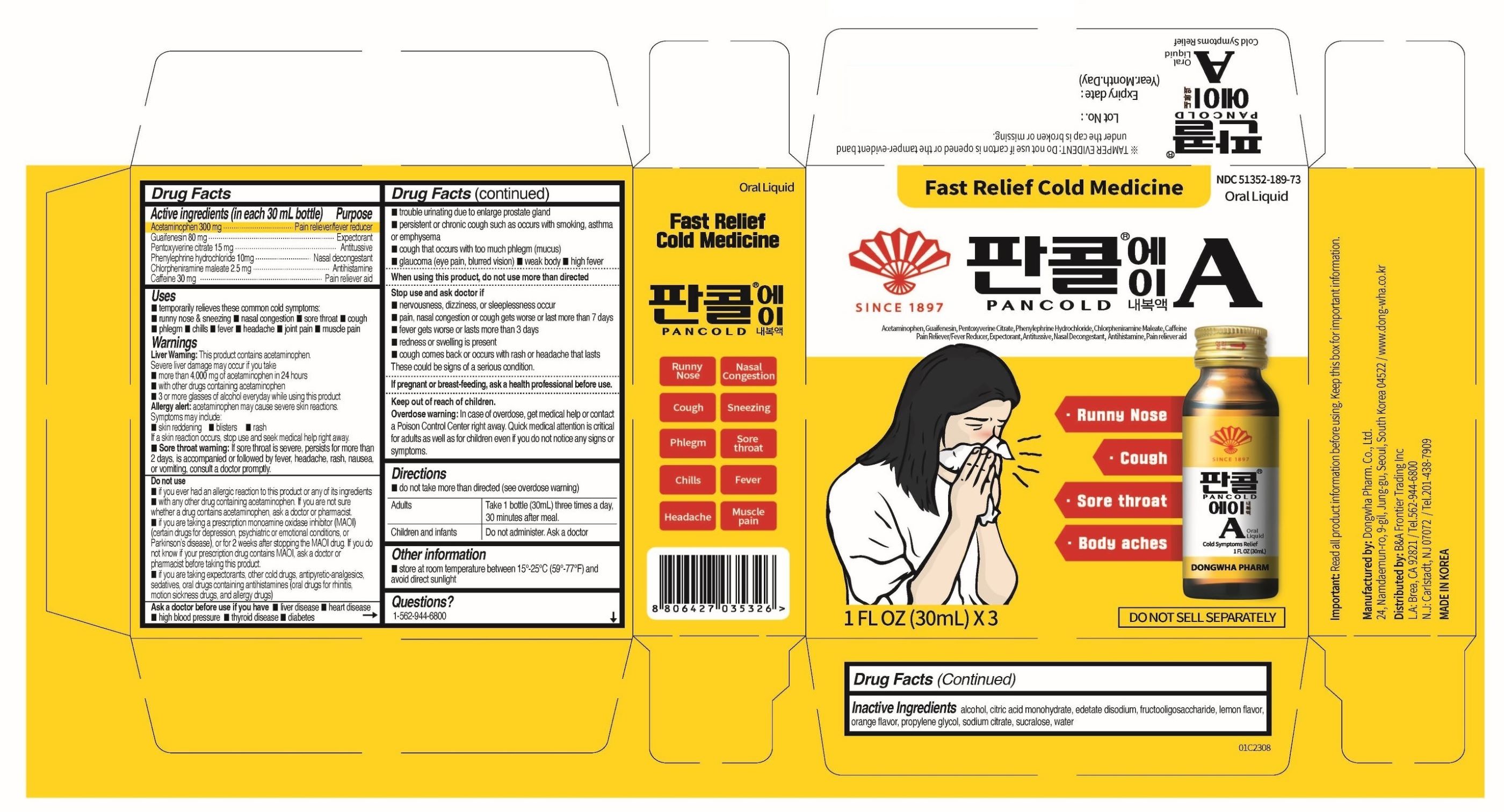 DRUG LABEL: PANCOLD A
NDC: 51352-189 | Form: LIQUID
Manufacturer: DONGWHA PHARM. CO. LTD.
Category: otc | Type: HUMAN OTC DRUG LABEL
Date: 20251231

ACTIVE INGREDIENTS: PENTOXYVERINE CITRATE 15 mg/30 mL; ACETAMINOPHEN 300 mg/30 mL; GUAIFENESIN 80 mg/30 mL; CHLORPHENIRAMINE MALEATE 2.5 mg/30 mL; CAFFEINE 30 mg/30 mL; PHENYLEPHRINE HYDROCHLORIDE 10 mg/30 mL
INACTIVE INGREDIENTS: SODIUM CITRATE 32.4 mg/30 mL; SUCRALOSE 10 mg/30 mL; PROPYLENE GLYCOL; CITRIC ACID MONOHYDRATE 29 mg/30 mL; EDETATE DISODIUM 3 mg/30 mL; ALCOHOL 0.5 mL/30 mL; SACCHARUM OFFICINARUM STEM FRUCTOOLIGOSACCHARIDES 7.5 g/30 mL; WATER; ORANGE; LEMON

PANCOLD A ORAL SOLUTION

ACTIVE INGREDIENTS

Active ingredients (in each 30 mL bottle)

- Acetaminophen 300 mg
- Guaifenesin 80 mg
- Pentoxyverine citrate 15 mg
- Phenylephrine Hydrochloride 10 mg
- Chlorpheniramine maleate 2.5 mg
- Caffeine 30 mg

PURPOSE

Pain Reliever-Fever Reducer, Expectorant, Antitussive, Nasal Decongestant, Antihistamine, Pain reliever aid

INDICATIONS & USAGE

Uses temporarily relieves these common cold symptoms:

- runny nose & sneezing
- nasal congestion
- sore throat
- cough
- phlegm
- chills
- fever
- headache
- joint pain
- muscle pain

WARNINGS SECTION

Warnings

Liver Warning: This product contains acetaminophen. Severe liver damage may occur if you take

- more than 4,000 mg of acetaminophen in 24 hours
- with other drugs containing acetaminophen
- 3 or more glasses of alcohol everyday while using this product

Allergy alert: acetaminophen mat cause severe skin reactions. Symptoms may include:

- skin reddening
- blisters
- rash

If a skin reaction occurs, stop use and seek medical help right away.

- Sore throat warning: If sore throat is severe, persists for more than 2 days, is accompanied or followed by fever, headache, rash, nausea, or vomiting, consult a doctor promptly.

DO NOT USE

- if you ever had an allergic reaction to this product or any of its ingredients
- with any other drug containing acetaminophen. If you are not sure whether a drug contains acetaminophen, ask a doctor or pharmacist.
- If you are taking a prescription monoamine oxidase inhibitor (MAOI) (certain drugs for depression, psychiatric or emotional conditions, or Parkinson’s disease), or for 2 weeks after stopping the MAOI drug. If you do not know if your prescription drug contains MAOI, ask a doctor or pharmacist before taking this product.
- If you are taking expectorants, other cold drugs, antipyretic-analgesics, sedatives, oral drugs containing antihistamines (oral drugs for rhinitis, motion sickness drugs, and allergy drugs)

Ask a doctor before use if you have

- liver disease
- heart disease
- high blood pressure
- thyroid disease
- diabetes
- trouble urinating due to enlarge prostate gland
- persistent or chronic cough such as occurs with smoking, asthma or emphysema
- cough that occurs with too much phlegm (mucus)
- glaucoma (eye pain, blurred vision)
- weak body
- high fever

STOP USE

Stop use and ask doctor if

- nervousness, dizziness, or sleeplessness occur
- pain, nasal congestion or cough gets worse or last more than 7 days
- fever gets worse or lasts more than 3 days n redness or swelling is present
- cough comes back or occurs with rash or headache that lasts

These could be signs of a serious condition.

PREGNANCY OR BREAST FEEDING

If pregnant or breast-feeding, ask a health professional before use.

KEEP OUT OF REACH OF CHILDREN

OVERDOSAGE

Overdose warning: In case of overdose, get medical help or contact a Poison Control Center right away. Quick medical attention is critical for adults as well as for children even if you do not notice any signs or symptom.

DOSAGE & ADMINISTRATION

Directions

- do not take more than directed (see overdose warning)

Adults: | Take 1 bottle (30mL) three times a day, 30 minutes after meal.
Children and infants: | Do not administer. Ask a doctor.

STORAGE AND HANDLING

Other nformation

- store at room temperature between 15°-25°C (59°-77°F) and avoid direct sunlight

INACTIVE INGREDIENTS

- Inactive Ingredients: : alcohol, citric acid monohydrate, edetate disodium, fructooligosaccharide, lemon flavor, orange flavor, propylene glycol, sodium citrate, sucralose, water